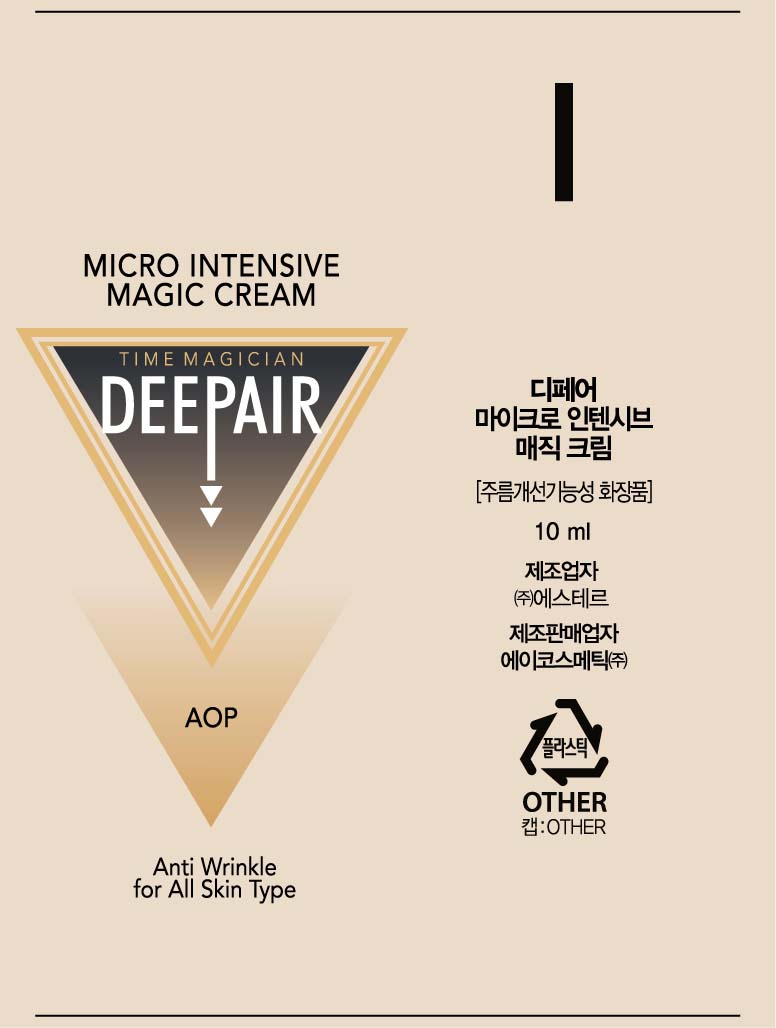 DRUG LABEL: DEEPAIR MICRO INTENSIVE MAGIC
NDC: 70961-0002 | Form: CREAM
Manufacturer: Acosmetic. Co.ltd
Category: otc | Type: HUMAN OTC DRUG LABEL
Date: 20160918

ACTIVE INGREDIENTS: ADENOSINE 0.04 g/100 mL
INACTIVE INGREDIENTS: WATER; HYALURONATE SODIUM; GLYCERIN

Drug Facts

ACTIVE INGREDIENT

Adenosine

INACTIVE INGREDIENT

Water, Glycerin, Propanediol, Ethylhexyl Palmitate, 1,2 Hexanediol, Limnanthes Alba (Meadowfoam) Seed Oil, Caprylic/Capric Triglyceride, Glyceryl Stearate, Cetearyl olivate, Betaine, Macadamia Integrifolia Seed Oil, Cetearyl Alcohol, Sodium Hyaluronate, Butyrospermum Parkii (Shea Butter), Acetyl Hexapeptide-8, Acetyl Octapeptide-3, Allantoin, Sorbitan olivate, Elaeis Guineensis (Palm) Oil, Elaeis Guineensis (Palm) Kernel Oil, Polysorbate 60, Arginine, Acrylates/C10-30 Alkyl Acrylate Crosspolymer, Hydroxypropyl Guar, Tocopheryl Acetate, Phenoxyethanol, Octanediol, Caprylyl Glycol, Ethylhexylglycerin, Disodium EDTA, Fragrance

PURPOSE

Skin Protectant - Anti-wrinkle

keep out of reach of the children

INDICATIONS AND USAGE

Apply to the skin before using DEEPAIR MICRO INTENSIVE MAGIC PATCH.

WARNINGS

1. If the following symptoms occur after product use, stop using the product immediately and consult a dermatologist (continuous use can exacerbate the symptoms).
1) Occurrence of red spots, swelling, itchiness, and other skin irritation
2) If the symptoms above occur after the application area is exposed to direct sunlight
2. Do not use on open wounds, eczema, and other skin irritations
3. Precaution for Storage and Handling
1) Close the lid after use
2) Keep out of reach of infants and children
3) Do not to store in a place with high/low temperature and exposed to direct sunlight

4. Use as avoiding eye areas.

DOSAGE AND ADMINISTRATION

for external use only